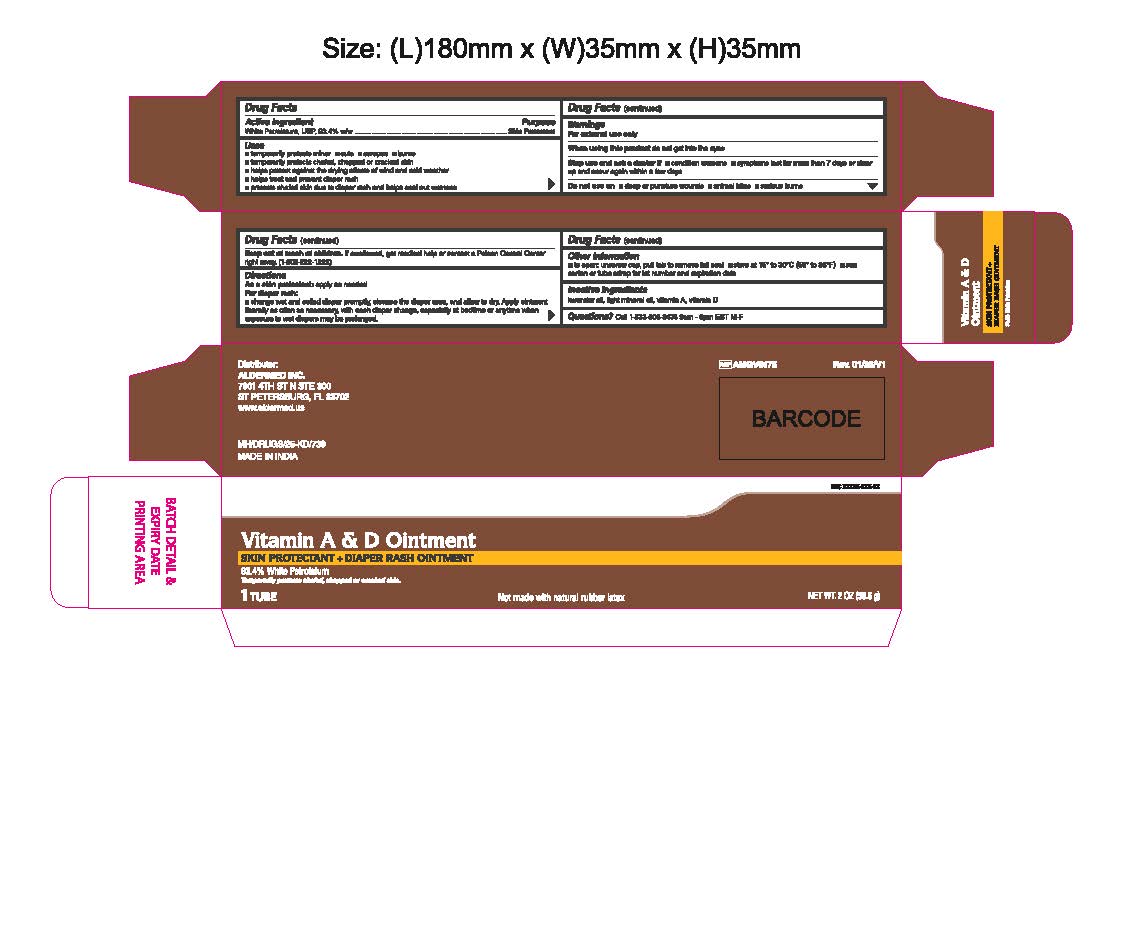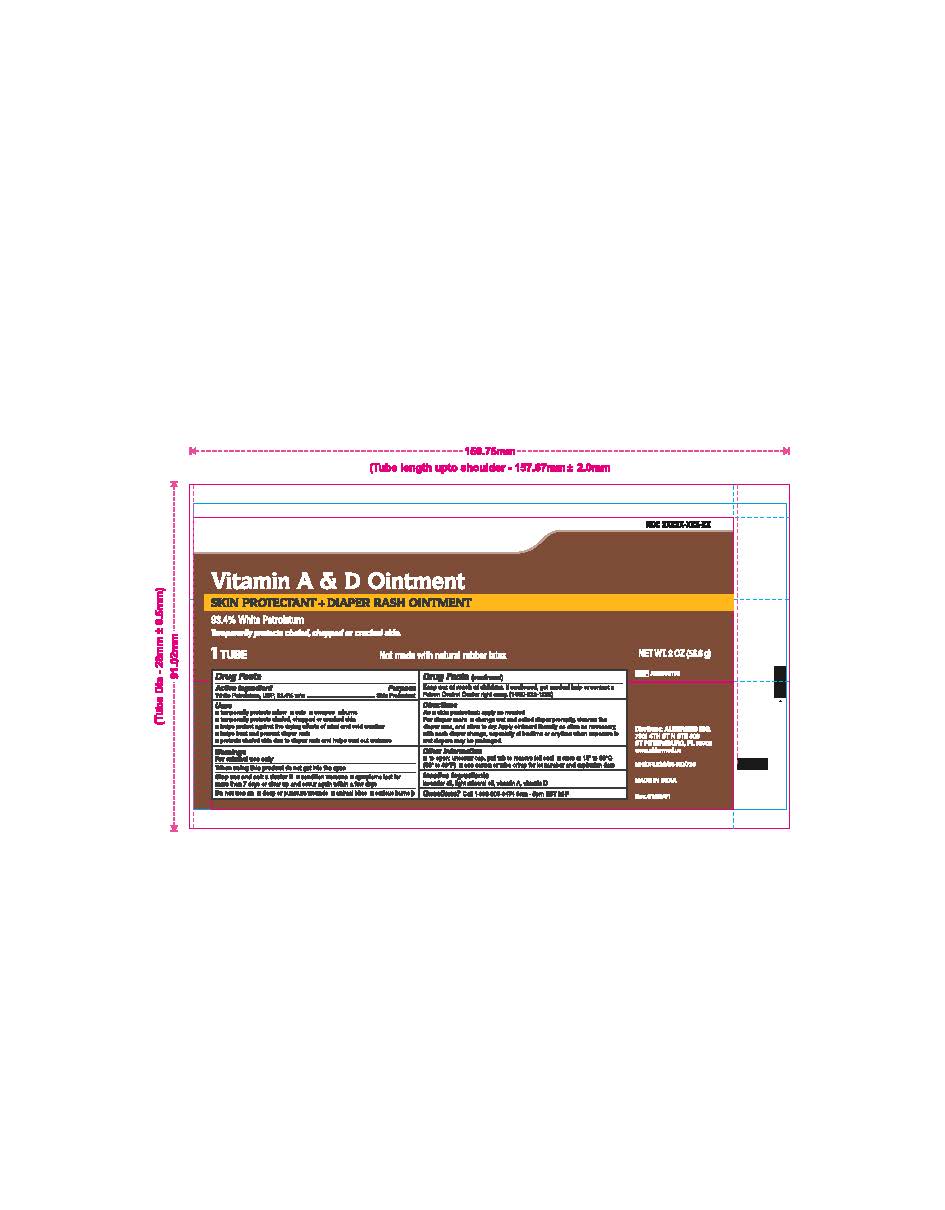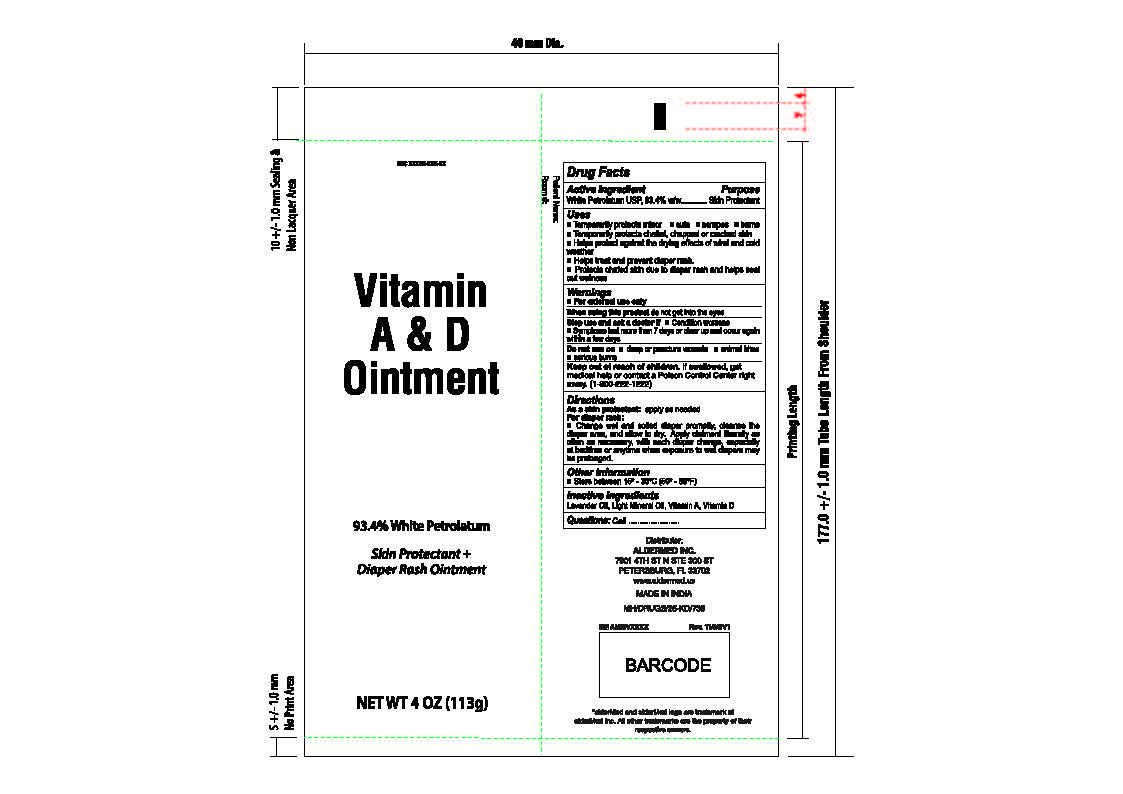 DRUG LABEL: Vitamin A and D
NDC: 87236-006 | Form: OINTMENT
Manufacturer: Aldermed Inc.
Category: otc | Type: HUMAN OTC DRUG LABEL
Date: 20260212

ACTIVE INGREDIENTS: WHITE PETROLATUM 934 mg/1 g
INACTIVE INGREDIENTS: LIGHT MINERAL OIL; VITAMIN A PALMITATE; VITAMIN D; LAVENDER OIL

Vitamin A&D ointment

Active ingredient (in each gram)

White petrolatum, USP, 93.4% w/w

Purpose

Skin protectant

Uses

■ Temporarily protects minor ■ cuts ■ scrapes ■ burns

■ Temporarily protects chafed, chapped or cracked skin
■ Helps protect against the drying effects of wind and cold weather
■ Helps treat and prevent diaper rash.
■ Protects chafed skin due to diaper rash and helps seal out wetness

Warnings

for external use only

Do not use on

- deep or puncture wounds
- animal bites
- serious burns

When using this product

- do not get into eyes

Stop use and ask a doctor if

- condition worsens
- if symptoms last for more than 7 days or clear up and occur again within a few days

Keep out of reach of children.

If swallowed, get medical help or contact a Poison Control Center right away (1-800-222-1222)

Directions

As a skin protectant:apply as needed
For diaper rash:
■ Change wet and soiled diaper promptly, cleanse the diaper area, and allow to dry. Apply ointment liberally as often as necessary, with each diaper change, especially at bedtime or anytime when exposure to wet diapers may be prolonged.

Other information

■ to open: unscrew cap, pull tab to remove foil seal ■ store at 15° to 30°C (59° to 86°F)

■ see carton or tube crimp for lot number and expiration date

Inactive ingredients

lavender oil, light mineral oil, vitamin A palmitate, vitamin D

Questions

Call 1-833-605-8474 9 am-5pm EST M-F